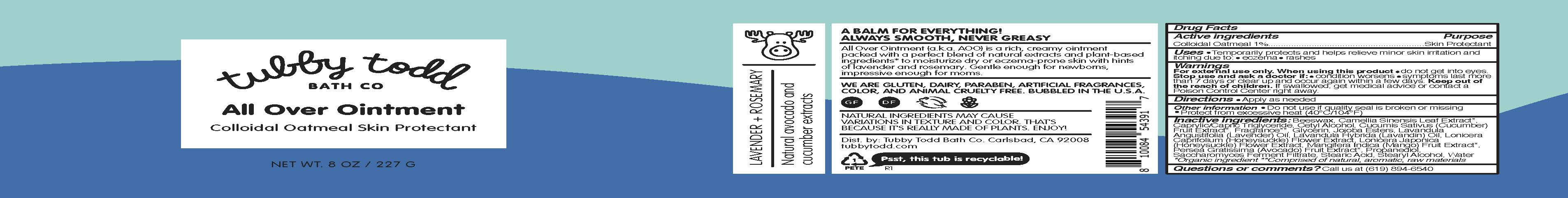 DRUG LABEL: All Over Lavender Rosemary
NDC: 73088-303 | Form: OINTMENT
Manufacturer: Tubby Todd
Category: otc | Type: HUMAN OTC DRUG LABEL
Date: 20241223

ACTIVE INGREDIENTS: OATMEAL 1 g/100 g
INACTIVE INGREDIENTS: CETYL ALCOHOL; LONICERA JAPONICA FLOWER; CAPRYLIC/CAPRIC TRIGLYCERIDE; LAVANDULA ANGUSTIFOLIA (LAVENDER) OIL; PROPANEDIOL; SACCHAROMYCES LYSATE; MANGIFERA INDICA (MANGO) FRUIT; AVOCADO; BEESWAX; CUCUMIS SATIVUS (CUCUMBER) FRUIT; GLYCERIN; LAVANDULA HYBRIDA OIL; STEARIC ACID; WATER; STEARYL ALCOHOL; CAMELLIA SINENSIS LEAF; HYDROLYZED JOJOBA ESTERS; LONICERA CAPRIFOLIUM FLOWER

All Over Ointment (Lavender Rosemary)

Active ingredients

Colloidal Oatmeal 1%

Purpose

Skin protectant

Uses

• Temporarily protects and helps relieve minor skin irritation and itching due to: • eczema • rashes

Warnings

For external use only.

When using this product

• do not get into eyes.

Stop use and ask a doctor if:

• condition worsens • symptoms last more than 7 days or clear up and occur again within a few days.

Keep out of reach of children.

If swallowed, get medical advice or contact a Poison Control Center right away.

Directions

• Apply as needed

Other information

• Do not use if quality seal is broken or missing
• Protect from excessive heat (40°C/104°F)

Inactive ingredients

Beeswax, Camellia Sinensis Leaf Extract*, Caprylic/Capric Triglyceride, Cetyl Alcohol, Cucumis Sativus (Cucumber) Fruit Extract*, Fragrance**, Glycerin, Jojoba Esters, Lavandula Angustifolia (Lavender) Oil, Lavandula Hybrida (Lavandin) Oil, Lonicera Caprifolium (Honeysuckle) Flower Extract, Lonicera Japonica (Honeysuckle) Flower Extract, Mangifera Indica (Mango) Fruit Extract*, Persea Gratissima (Avocado) Fruit Extract*, Propanediol, Saccharomyces Ferment Filtrate, Stearic Acid, Stearyl Alcohol, Water
*Organic ingredient **Comprised of natural, aromatic, raw materials

Questions?

Call us at (619) 894-6560